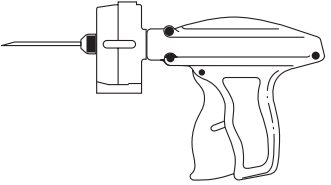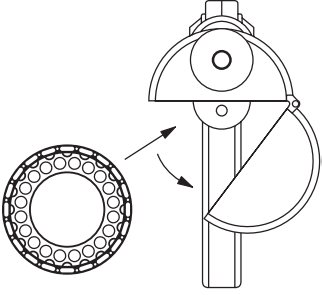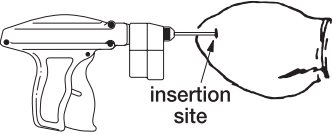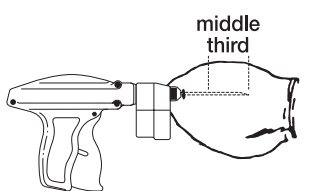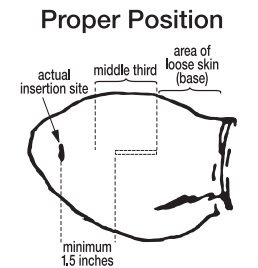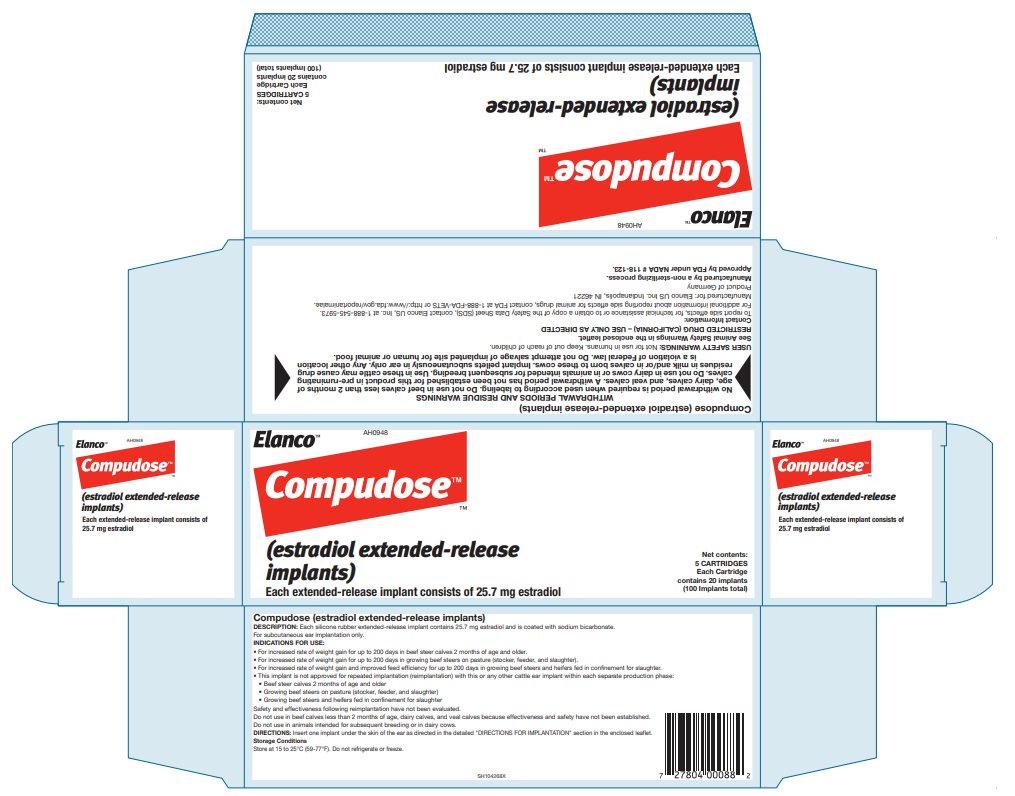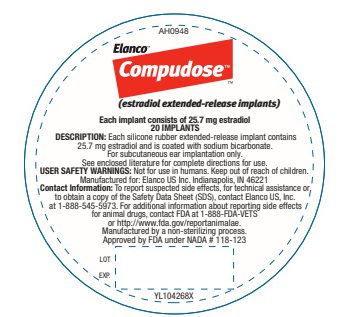 DRUG LABEL: Compudose
NDC: 58198-0327 | Form: IMPLANT
Manufacturer: Elanco US Inc.
Category: animal | Type: OTC ANIMAL DRUG LABEL
Date: 20251028

ACTIVE INGREDIENTS: estradiol 25.7 mg/1 1

AH0948

Elanco™

Compudose™

(estradiol extended-release implants)

Each extended-release implant consists of 25.7 mg estradiol

DESCRIPTION:

Each Compudose (estradiol extended-release implant) silicone rubber implant contains 25.7 mg estradiol and is coated with sodium bicarbonate.

For subcutaneous ear implantation only.

INDICATIONS FOR USE:

- For increased rate of weight gain for up to 200 days in beef steer calves 2 months of age and older.
- For increased rate of weight gain for up to 200 days in growing beef steers on pasture (stocker, feeder, and slaughter).
- For increased rate of weight gain and improved feed efficiency for up to 200 days in growing beef steers and heifers fed in confinement for slaughter.
- This implant is not approved for repeated implantation (reimplantation) with this or any other cattle ear implant within each separate production phase:
  - Beef steer calves 2 months of age and older
  - Growing beef steers on pasture (stocker, feeder, and slaughter)
  - Growing beef steers and heifers fed in confinement for slaughter

Safety and effectiveness following reimplantation have not been evaluated.

Do not use in beef calves less than 2 months of age, dairy calves, and veal calves because effectiveness and safety have not been established.

Do not use in animals intended for subsequent breeding or in dairy cows.

DIRECTIONS:

Insert one implant under the skin of the ear as directed in the detailed "DIRECTIONS FOR IMPLANTATION" below.

WITHDRAWAL PERIODS AND RESIDUE WARNINGS

No withdrawal period is required when used according to labeling. Do not use in beef calves less than 2 months of age, dairy calves, and veal calves. A withdrawal period has not been established for this product in pre-ruminating calves. Do not use in dairy cows or in animals intended for subsequent breeding. Use in these cattle may cause drug residues in milk and/or in calves born to these cows. Implant pellets subcutaneously in ear only. Any other location is a violation of Federal law. Do not attempt salvage of implanted site for human or animal food.

USER SAFETY WARNINGS:

Not for use in humans.

Keep out of reach of children.

ANIMAL SAFETY WARNINGS:

Increased sexual activity (bulling, riding and excitability) has been reported in animals implanted with Compudose. Implanted animals should be observed for such signs particularly during the first few days after implanting and animals being excessively ridden (bullers) should be removed to prevent physical injury.

Vaginal and rectal prolapse have been reported in heifers implanted with Compudose.

Udder development, swollen or enlarged vulva and high tailheads may be observed in implanted heifers.

DIRECTIONS FOR IMPLANTATION:

A Compudose (estradiol extended-release implant) or Encore (estradiol extended-release implant) Implanter must be used to implant cattle.

COMPUDOSE/ENCORE IMPLANTER

Insert one implant under the skin of the ear.

1. Confine animal in a squeeze chute.
2. To reduce the possibility of infection and resulting implant loss, hygienic and antiseptic procedures should be followed during implantation. The ear should be clean and dry. The skin should be cleansed with a suitable antiseptic soap and dried prior to implanting. This is particularly important if the ears are contaminated with urine or feces.
3. To load the Compudose/Encore™ Implanter remove the cartridge from the package, release the latch on the magazine, open and insert the cartridge. (Figure 1)
  Close the magazine and latch. Advance the cartridge to the next implant by inserting the thumb into the magazine opening and turning the cartridge to the next stop.
  Use a sharp needle. The needle should be cleaned and sterilized between each injection by wiping the exterior with a sponge, cloth, or gauze saturated with an appropriate disinfectant.
  Figure 1

4. The implant should be deposited under the skin on the back side of the middle third of the ear. It should be placed between the skin and cartilage, avoiding major blood vessels.
  Grasping the tip of the ear with one hand and the implanter in the other, penetrate the skin in the outer third of the ear. (see Figure 2)

Figure 2

IMPORTANT: Do not penetrate cartilage.

5. Upon penetration, the needle should be fully inserted (Figure 3) between the skin and cartilage, avoiding major blood vessels. Full insertion of the needle is important to maximize implant retention.

Figure 3

6. Pull the needle back as the implant is being deposited by squeezing the lever on the implanter grip. Figure 4 shows the implant in proper position in the middle third of the ear where the skin is tight.
7. Periodically remove the needle from the device and wash it in water. Before reusing, the needle should be disinfected and allowed to dry after shaking vigorously to remove excess water or disinfectant.

Figure 4

To maximize implant retention:

A. Fully insert the needle.
B. Deposit the implant in the middle third of the ear where the skin is tight.
C. Do not deposit the implant where the skin is loose in the third of the ear closest to the head.

The needle has been scientifically designed to maximize retention. When it becomes dull, use a new needle. If the needle is resharpened, sharpen only the point.

Failure to follow antiseptic implanting procedures, particularly when the ears are contaminated with fecal material, may result in infection and excessive implant loss. Implanting cattle during wet weather may increase infection and implant loss.

Carefully check the ears for implant loss approximately 4 weeks after implantation. If loss occurs, reimplant using recommended procedures.

How Supplied:

Compudose Implants are supplied in cartridges of 20 implants each.

Storage Conditions

Store at 15 to 25°C (59-77°F). Do not refrigerate or freeze.

Approved by FDA under NADA # 118-123

Manufactured by a non-sterilizing process.

RESTRICTED DRUG (CALIFORNIA) – USE ONLY AS DIRECTED

Compudose, Encore, Elanco and the diagonal bar logo are trademarks of Elanco or its affiliates.

© 2025 Elanco or its affiliates

Manufactured for: Elanco US Inc.
Indianapolis, IN 46221
Product of Germany

Contact Information: To report side effects, for technical assistance or to obtain a copy of the Safety Data Sheet (SDS), contact Elanco US Inc., at 1-888-545-5973. For additional information about reporting side effects for animal drugs, contact FDA at 1-888-FDA-VETS or http://www.fda.gov/reportanimalae.

August 2025 PA104268X

Principal Display Panel - Compudose Carton Label

Elanco™ AH0948

Compudose™

™

(estradiol extended-release implants)

Each extended-release implant consists of 25.7 mg estradiol

Net contents:
5 CARTRIDGES
Each Cartridge
contains 20 implants
(100 Implants total)

Principal Display Panel - Compudose Cartridge Label

AH0948

Elanco™

Compudose™

™

(estradiol extended-release implants)

Each implant consists of 25.7 mg estradiol

20 IMPLANTS